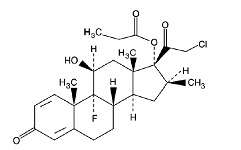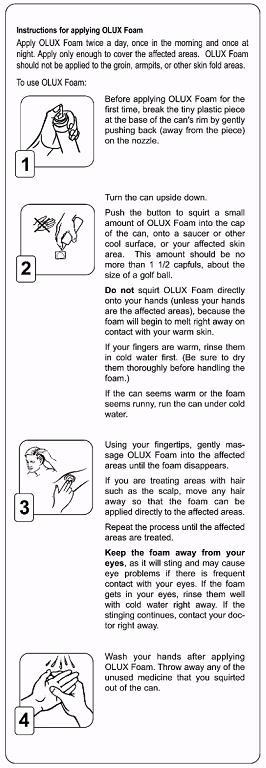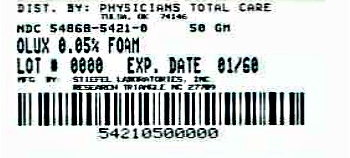 DRUG LABEL: OLUX
NDC: 54868-5421 | Form: AEROSOL, FOAM
Manufacturer: Physicians Total Care, Inc.
Category: prescription | Type: HUMAN PRESCRIPTION DRUG LABEL
Date: 20120502

ACTIVE INGREDIENTS: CLOBETASOL PROPIONATE 0.5 mg/1 g
INACTIVE INGREDIENTS: CETYL ALCOHOL; ANHYDROUS CITRIC ACID; ALCOHOL; POLYSORBATE 60; POTASSIUM CITRATE; PROPYLENE GLYCOL; WATER; STEARYL ALCOHOL

Olux® (clobetasol propionate) Foam, 0.05%

Rx Only

For Dermatologic Use Only

Not for Ophthalmic Use

DESCRIPTION

Olux Foam contains clobetasol propionate, USP, a synthetic corticosteroid, for topical dermatologic use. Clobetasol, an analog of prednisolone, has a high degree of glucocorticoid activity and a slight degree of mineralocorticoid activity.

Clobetasol propionate is pregna-1,4-diene-3,20-dione, 21-chloro-9-fluoro-11-hydroxy-16-methyl-17-(1-oxopropoxy)-, (11β,16β)-, with the empirical formula C25H32CIFO5, a molecular weight of 466.97. The following is the chemical structure:

clobetasol propionate

Clobetasol propionate is a white or almost white, odorless, crystalline powder and is insoluble in water.

Olux® (clobetasol propionate) Foam, 0.05%, contains 0.5 mg clobetasol propionate, USP, per gram in a thermolabile hydroethanolic foam vehicle consisting of cetyl alcohol, citric acid, ethanol (60%), polysorbate 60, potassium citrate, propylene glycol, purified water, and stearyl alcohol pressurized with a hydrocarbon (propane/butane) propellant.

CLINICAL PHARMACOLOGY

Like other topical corticosteroids, clobetasol propionate foam has anti-inflammatory, antipruritic, and vasoconstrictive properties. The precise mechanism of the anti-inflammatory activity of topical steroids in the treatment of steroid-responsive dermatoses, in general, is uncertain. However, corticosteroids are thought to act by the induction of phospholipase A2 inhibitory proteins, collectively called lipocortins. It is postulated that these proteins control the biosynthesis of potent mediators of inflammation such as prostaglandins and leukotrienes by inhibiting the release of their common precursor arachidonic acid. Arachidonic acid is released from membrane phospholipids by phospholipase A2.

Pharmacokinetics:

Topical corticosteroids can be absorbed from intact healthy skin. The extent of percutaneous absorption of topical corticosteroids is determined by many factors, including the vehicle and the integrity of the epidermal barrier. Occlusion, inflammation and/or other disease processes in the skin may also increase percutaneous absorption.

Once absorbed through the skin, topical corticosteroids are handled through pharmacokinetic pathways similar to systemically administered corticosteroids. Due to the fact that circulating levels are well below the level of detection, the use of pharmacodynamic endpoints for assessing the systemic exposure of topical corticosteroids is necessary. They are metabolized, primarily in the liver, and are then excreted by the kidneys. In addition, some corticosteroids and their metabolites are also excreted in the bile.

CLINICAL STUDIES

A well-controlled clinical study evaluated 188 subjects with moderate to severe scalp psoriasis. Subjects were treated twice daily for 2 weeks with one of four treatments: Olux Foam, Vehicle foam, a commercially available clobetasol propionate solution (Temovate® Scalp Application), or Vehicle solution. The efficacy of Olux Foam in treating scalp psoriasis at the end of the 2 weeks' treatment was superior to that of Vehicle (foam and solution), and was comparable to that of the commercially available Scalp Application. See Table 1 below.

Table 1: Efficacy results from a controlled clinical trial in scalp psoriasis
 | Olux Foam n (%) | Vehicle Foam n (%)
Total number of subjects | 62 | 31
Subjects with Treatment Success | 39 (63) | 1 (3)
Subjects with Parameter Clear at Endpoint (Scalp Psoriasis)
Scaling - Clear at Endpoint | 42 (68) | 3 (10)
Erythema - Clear at Endpoint | 27 (44) | 2 (6)
Plaque Thickness - Clear at Endpoint | 41 (66) | 3 (10)

Another well-controlled clinical study evaluated 279 subjects with mild to moderate plaque-type psoriasis (mean Body Surface Area at baseline was 6.7% with a range from 1% to 20%) of non-scalp regions. Subjects were treated twice daily for 2 weeks with Olux Foam or Vehicle foam. The face and intertriginous areas were excluded from treatment. The efficacy of Olux Foam in treating non-scalp psoriasis at the end of 2 weeks’ treatment was superior to that of Vehicle foam. See Table 2 below.

Table 2: Efficacy results from a controlled clinical trial in non-scalp psoriasis
 | Olux Foam n (%) | Vehicle Foam n (%)
Total number of subjects | 139 | 140
Subjects with Treatment Success | 39 (28) | 4 (3)
Physician's Static Global Assessment - Clear or Almost Clear at Endpoint | 94 (68) | 30 (21)
Scaling - Clear or Almost Clear at Endpoint | 101 (73) | 42 (30)
Erythema - Clear or Almost Clear at Endpoint | 88 (63) | 35 (25)
Plaque Thickness - Clear at Endpoint | 44 (32) | 5 (4)

INDICATIONS AND USAGE

Olux Foam is a super-potent topical corticosteroid indicated for short-term topical treatment of the inflammatory and pruritic manifestations of moderate to severe corticosteroid-responsive dermatoses of the scalp, and for short-term topical treatment of mild to moderate plaque-type psoriasis of non-scalp regions excluding the face and intertriginous areas.

Treatment beyond 2 consecutive weeks is not recommended and the total dosage should not exceed 50 g per week because of the potential for the drug to suppress the hypothalamic-pituitary-adrenal (HPA) axis. In a controlled pharmacokinetic study, some subjects experienced reversible suppression of the adrenals following 14 days of OLUX Foam therapy (See ADVERSE REACTIONS).

Use in children under 12 years of age is not recommended.

CONTRAINDICATIONS

Olux Foam is contraindicated in patients who are hypersensitive to clobetasol propionate, to other corticosteroids, or to any ingredient in this preparation.

PRECAUTIONS

General

Clobetasol propionate is a super-potent topical corticosteroid that has been shown to suppress the adrenals at 7.0 g of Olux Foam per day. Lesser amounts of Olux Foam were not studied. Systemic absorption of topical corticosteroids has caused reversible adrenal suppression with the potential for glucocorticosteroid insufficiency after withdrawal of treatment. Manifestations of Cushing’s syndrome, hyperglycemia, and glucosuria can also be produced in some patients by systemic absorption of topical corticosteroids while on treatment.

Conditions which augment systemic absorption include the application of more potent steroids, use over large surface areas, prolonged use, and the addition of occlusive dressings.

Patients applying a topical steroid to a large surface area or to areas under occlusion should be evaluated periodically for evidence of adrenal suppression. If adrenal suppression is noted, an attempt should be made to withdraw the drug, to reduce the frequency of application, or to substitute a less potent steroid.

Recovery of HPA axis function is generally prompt upon discontinuation of topical corticosteroids. Infrequently, signs and symptoms of glucocorticosteroid insufficiency may occur requiring supplemental systemic corticosteroids. For information on systemic supplementation, see prescribing information for those products.

Pediatric patients may be more susceptible to systemic toxicity from equivalent doses due to their larger skin surface to body mass ratios. See PRECAUTIONS -Pediatric Use.

If irritation develops, Olux Foam should be discontinued and appropriate therapy instituted. Allergic contact dermatitis with corticosteroids is usually diagnosed by observing failure to heal rather than by noting a clinical exacerbation, as with most topical products not containing corticosteroids. Such an observation should be corroborated with appropriate diagnostic patch testing.

In the presence of dermatological infections, the use of an appropriate antifungal or antibacterial agent should be instituted. If a favorable response does not occur promptly, use of Olux Foam should be discontinued until the infection has been adequately controlled.

Information for Patients

Patients using topical corticosteroids should receive the following information and instructions:

1. This medication is to be used as directed by the physician and should not be used longer than the prescribed time period. It is for external use only. Avoid contact with the eyes.
2. This medication should not be used for any disorder other than that for which it was prescribed.
3. The treated area should not be bandaged or otherwise covered or wrapped, so as to be occlusive unless directed by the physician.
4. Patients should report to their physician any signs of local adverse reactions.

Laboratory Tests

The following tests may be helpful in evaluating patients for adrenal suppression:

ACTH stimulation test

A.M. plasma cortisol test

Urinary free cortisol test

Carcinogenesis, Mutagenesis, and Impairment of Fertility

Long-term animal studies have not been performed to evaluate the carcinogenic potential of clobetasol propionate.

Clobetasol propionate was non-mutagenic in three different test systems: the Ames test, the Saccharomyces cerevisiae gene conversion assay, and the E. coli B WP2 fluctuation test.

Studies in the rat following subcutaneous administration of clobetasol propionate at dosage levels up to 0.05 mg/kg per day revealed that the females exhibited an increase in the number of resorbed embryos and a decrease in the number of living fetuses at the highest dose.

Pregnancy

Teratogenic Effects

Pregnancy Category C

Corticosteroids have been shown to be teratogenic in laboratory animals when administered systemically at relatively low dosage levels. Some corticosteroids have been shown to be teratogenic after dermal application to laboratory animals.

Clobetasol propionate has not been tested for teratogenicity by the topical route; however, it is absorbed percutaneously, and when administered subcutaneously, it was a significant teratogen in both the rabbit and the mouse. Clobetasol propionate has greater teratogenic potential than steroids that are less potent.

Teratogenicity studies in mice using the subcutaneous route resulted in fetotoxicity at the highest dose tested (1 mg/kg) and teratogenicity at all dose levels tested down to 0.03 mg/kg. These doses are approximately 1.4 and 0.04 times, respectively, the human topical dose of Olux based on body surface area comparisons. Abnormalities seen included cleft palate and skeletal abnormalities.

In rabbits, clobetasol propionate was teratogenic at doses of 0.003 and 0.01 mg/kg. These doses are approximately 0.02 and 0.05 times, respectively, the human topical dose of Olux based on body surface area comparisons. Abnormalities seen included cleft palate, cranioschisis, and other skeletal abnormalities.

There are no adequate and well-controlled studies of the teratogenic potential of clobetasol propionate in pregnant women. Olux Foam should be used during pregnancy only if the potential benefit justifies the potential risk to the fetus.

Drugs of this class should not be used extensively on pregnant patients, in large amounts, or for prolonged periods of time.

Nursing Mothers

Systemically administered corticosteroids appear in human milk and could suppress growth, interfere with endogenous corticosteroid production, or cause other untoward effects. It is not known whether topical administration of corticosteroids could result in sufficient systemic absorption to produce detectable quantities in breast milk. Because many drugs are excreted in human milk, caution should be exercised when Olux Foam is administered to a nursing woman.

Pediatric Use

Safety and effectiveness of Olux Foam in pediatric patients have not been established; therefore, use in children under 12 years of age is not recommended. Because of a higher ratio of skin surface area to body mass, pediatric patients are at a greater risk than adults of adrenal suppression and Cushing’s syndrome when they are treated with topical corticosteroids. Pediatric patients are therefore at greater risk of adrenal insufficiency during and/or after withdrawal of treatment. Adverse effects including striae have been reported with inappropriate use of topical corticosteroids in infants and children.

Adrenal suppression, Cushing’s syndrome, linear growth retardation, delayed weight gain, and intracranial hypertension have been reported in children receiving topical corticosteroids. Manifestations of adrenal suppression in children include low plasma cortisol levels and absence of response to ACTH stimulation. Manifestations of intracranial hypertension include bulging fontanelles, headaches, and bilateral papilledema.

Geriatric Use

Clinical studies of Olux Foam did not include sufficient numbers of subjects aged 65 and over to determine whether they respond differently from younger subjects. Other reported clinical experience has not identified differences in responses between the elderly and younger patients. In general, dose selection for an elderly patient should be cautious, usually starting at the low end of the dosing range, reflecting the greater frequency of decreased hepatic, renal, or cardiac function, and of concomitant disease or other drug therapy.

ADVERSE REACTIONS

In a controlled pharmacokinetic study, 5 of 13 subjects experienced reversible suppression of the adrenals at any time during the 14 days of Olux Foam therapy to at least 20% of the body surface area. Of the 13 subjects studied, 1 of 9 with psoriasis were suppressed after 14 days and all 4 of the subjects with atopic dermatitis had abnormal cortisol levels indicative of adrenal suppression at some time after starting therapy with Olux Foam. (See Table 3 below.)

Table 3: Subjects with reversible HPA axis suppression at any time during treatment
Dermatosis | Olux Foam
Psoriasis | 1 of 9
Atopic Dermatitis | 4 of 4

Systemic absorption of topical corticosteroids has produced reversible adrenal suppression, manifestations of Cushing’s syndrome, hyperglycemia, and glucosuria in some patients (see PRECAUTIONS).

In a controlled clinical trial (188 subjects) with Olux Foam in subjects with psoriasis of the scalp, there were no localized scalp adverse reactions reported in the Olux Foam treated subjects. In two controlled clinical trials (360 subjects) with Olux Foam in subjects with psoriasis of non-scalp regions, localized adverse events that occurred in the Olux Foam treated subjects included application site burning (10%), application site dryness (< 1%), and other application site reactions (4%).

In larger controlled trials with other clobetasol propionate formulations, the most frequently reported local adverse reactions have included burning, stinging, irritation, pruritus, erythema, folliculitis, cracking and fissuring of the skin, numbness of the fingers, skin atrophy, and telangiectasia (all less than 2%).

The following additional local adverse reactions have been reported with topical corticosteroids, but they may occur more frequently with the use of occlusive dressings and higher potency corticosteroids such as Olux Foam. These reactions are listed in an approximate decreasing order of occurrence: dryness, hypertrichosis, acneiform eruptions, hypopigmentation, perioral dermatitis, allergic contact dermatitis, maceration of the skin, secondary infection, striae, and miliaria.

OVERDOSAGE

Topically applied Olux Foam can be absorbed in sufficient amounts to produce systemic effects. See PRECAUTIONS.

DOSAGE AND ADMINISTRATION

Note: For proper dispensing of foam, hold the can upside down and depress the actuator.

Olux Foam should be applied to the affected area twice daily, once in the morning and once at night. Invert the can and dispense a small amount of Olux Foam (up to a maximum of a golf-ball-size dollop or one and a half capfuls) into the cap of the can, onto a saucer or other cool surface, or to the lesion, taking care to avoid contact with the eyes. Dispensing directly onto hands is not recommended (unless the hands are the affected area), as the foam will begin to melt immediately upon contact with warm skin. When applying Olux Foam to a hair-bearing area, move the hair away from the affected area so that the foam can be applied to each affected area. Pick up small amounts with fingertips and gently massage into affected area until the foam disappears. Repeat until entire affected area is treated.

Apply the smallest amount possible that sufficiently covers the affected area(s). No more than one and a half capfuls of foam should be used at each application. Do not apply to face or intertriginous areas.

Olux Foam is a super-high-potency topical corticosteroid; therefore, treatment should be limited to 2 consecutive weeks and amounts greater than 50 g/week should not be used. Use in pediatric patients under 12 years of age is not recommended.

Unless directed by a physician, Olux Foam should not be used with occlusive dressings.

HOW SUPPLIED

Olux Foam is supplied as follows:

- 50 g aluminum can NDC 54868-5421-0

Store at controlled room temperature 68–77°F (20–25°C).

WARNING

FLAMMABLE. AVOID FIRE, FLAME OR SMOKING DURING AND IMMEDIATELY FOLLOWING APPLICATION. Keep out of reach of children. Contents under pressure. Do not puncture or incinerate container. Do not expose to heat or store at temperatures above 120°F (49°C).

Manufactured for

Stiefel Laboratories, Inc.
Research Triangle Park, NC 27709

For additional information:

1-888-784-3335 (STIEFEL)

or visit

www.olux.com

OLX:1PI

OLUX is a registered trademark of Stiefel Laboratories, Inc.

©2011 Stiefel Laboratories, Inc.

March 2011

Additional barcode labeling by:
Physicians Total Care, Inc.
Tulsa, Oklahoma 74146

Principal Display Panel

NDC 54868-5421-0

Olux®

(clobetasol propionate) Foam, 0.05%

50 g

Rx only

FOR DERMATOLOGIC USE ONLY.

NOT FOR OPHTHALMIC USE.

Invert can and then press firmly to dispense.

Description: Olux® (clobetasol propionate) foam, 0.05%, contains 0.5 mg clobetasol propionate, USP, per gram in a thermolabile hydroethanolic foam vehicle consisting of cetyl alcohol, citric acid, ethanol (60%), polysorbate 60, potassium citrate, propylene glycol, purified water, and stearyl alcohol pressurized with a hydrocarbon (propate/butane) propellant.

Dosage: Use only as prescribed by your physician. See package insert for full prescribing information.

Warning: FLAMMABLE. AVOID FIRE, FLAME, OR SMOKING DURING AND IMMEDIATELY FOLLOWING APPLICATION.

Keep away from eyes. Keep out of reach of children.

Contents under pressure. Do not puncture or incinerate container. Do not expose to heat or store at temperatures above 120°F (49°C).

Store at controlled room temperature, 68°-77°F (20°-25°C).

CFC FREE